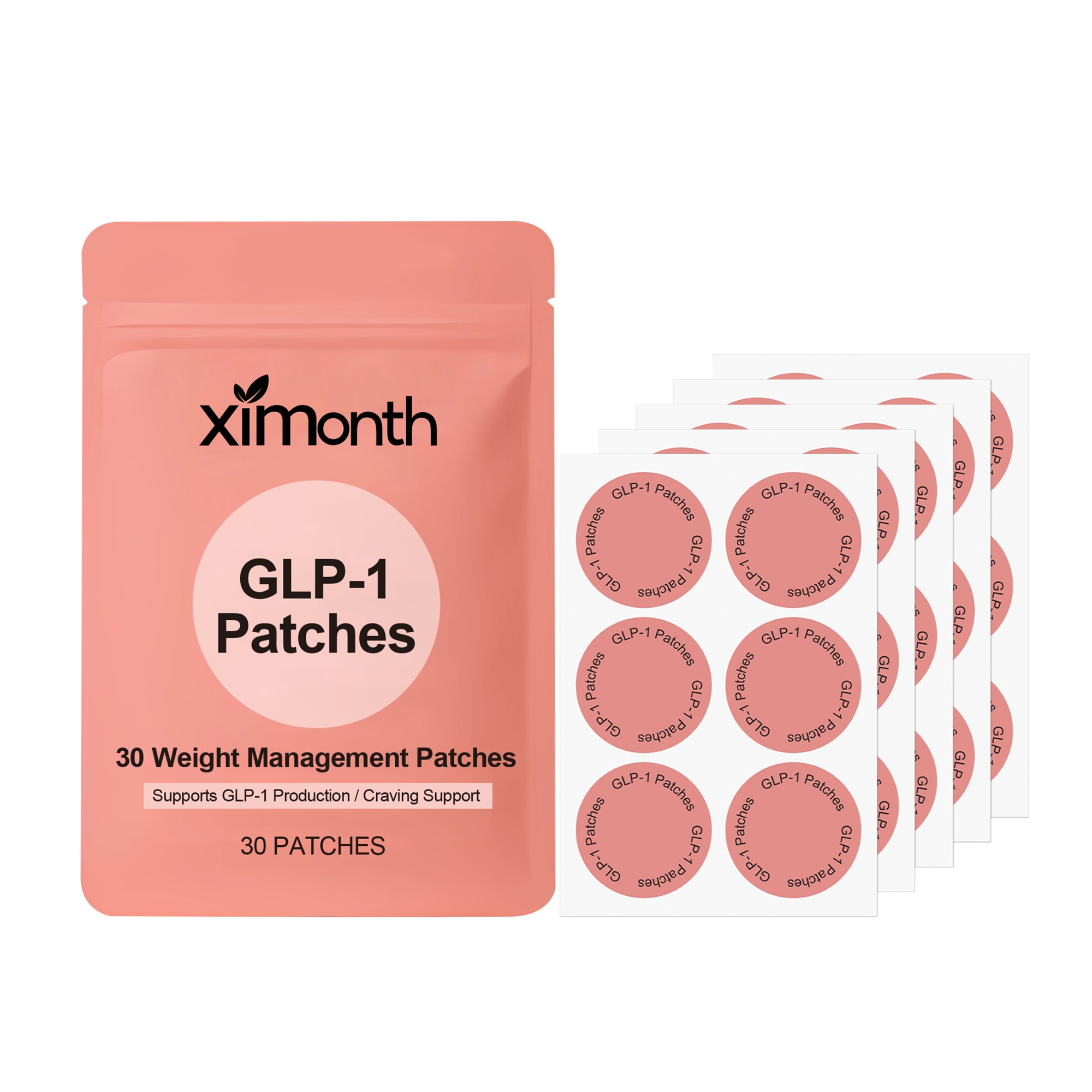 DRUG LABEL: XIMONTH GLP-1 Patches
NDC: 84989-009 | Form: PATCH
Manufacturer: Shantou Ximonth Biotechnology Co., Ltd.
Category: otc | Type: HUMAN OTC DRUG LABEL
Date: 20251126

ACTIVE INGREDIENTS: ACETYL HEXAPEPTIDE-8 AMIDE 0.006 mg/30 mg; ROSE OIL 0.006 mg/30 mg
INACTIVE INGREDIENTS: GLYCERIN 1.5 mg/30 mg; HYDROXYETHYL CELLULOSE, UNSPECIFIED 0.15 mg/30 mg; WATER 28.179 mg/30 mg; 1,2-HEXANEDIOL 0.15 mg/30 mg; ALLANTOIN 0.006 mg/30 mg; EDETATE DISODIUM 0.003 mg/30 mg

ACTIVE INGREDIENT

ACETYL HEXAPEPTIDE-8 AMIDE、ROSE OIL

WHEN USING

Clean and dry your skin, apply the product to your upper arms, abdomen or thighs, press gently to ensure adhesion, leave it on for 6-8 hours and then remove.

PURPOSE

Reduce fat; Promote weight loss; Suppress appetite; Control weight; Increase energy; Promote metabolism

WARNINGS

Please keep out of reach of children. Do not swallow.Please clean your hands before use to ensure the best results from the product. Discontinue use if signs of irritation or rash occur. Store in a cool and dry place.

DO NOT USE

Discontinue use if signs of irritation or rash occur.

STOP USE

Discontinue use if signs of irritation or rash occur.

KEEP OUT OF REACH OF CHILDREN

Please keep out of reach of children. Do not swallow.

STORAGE AND HANDLING

Store in a cool and dry place.

INACTIVE INGREDIENT

WATER、GLYCERIN、HYDROXYETHYL CELLULOSE, UNSPECIFIED、1,2-HEXANEDIOL、ALLANTOIN、EDETATE DISODIUM

INDICATIONS AND USAGE

Clean and dry your skin, apply the product to your upper arms, abdomen or thighs, press gently to ensure adhesion, leave it on for 6-8 hours and then remove.

DOSAGE AND ADMINISTRATION

Clean and dry your skin, apply the product to your upper arms, abdomen or thighs, press gently to ensure adhesion, leave it on for 6-8 hours and then remove.